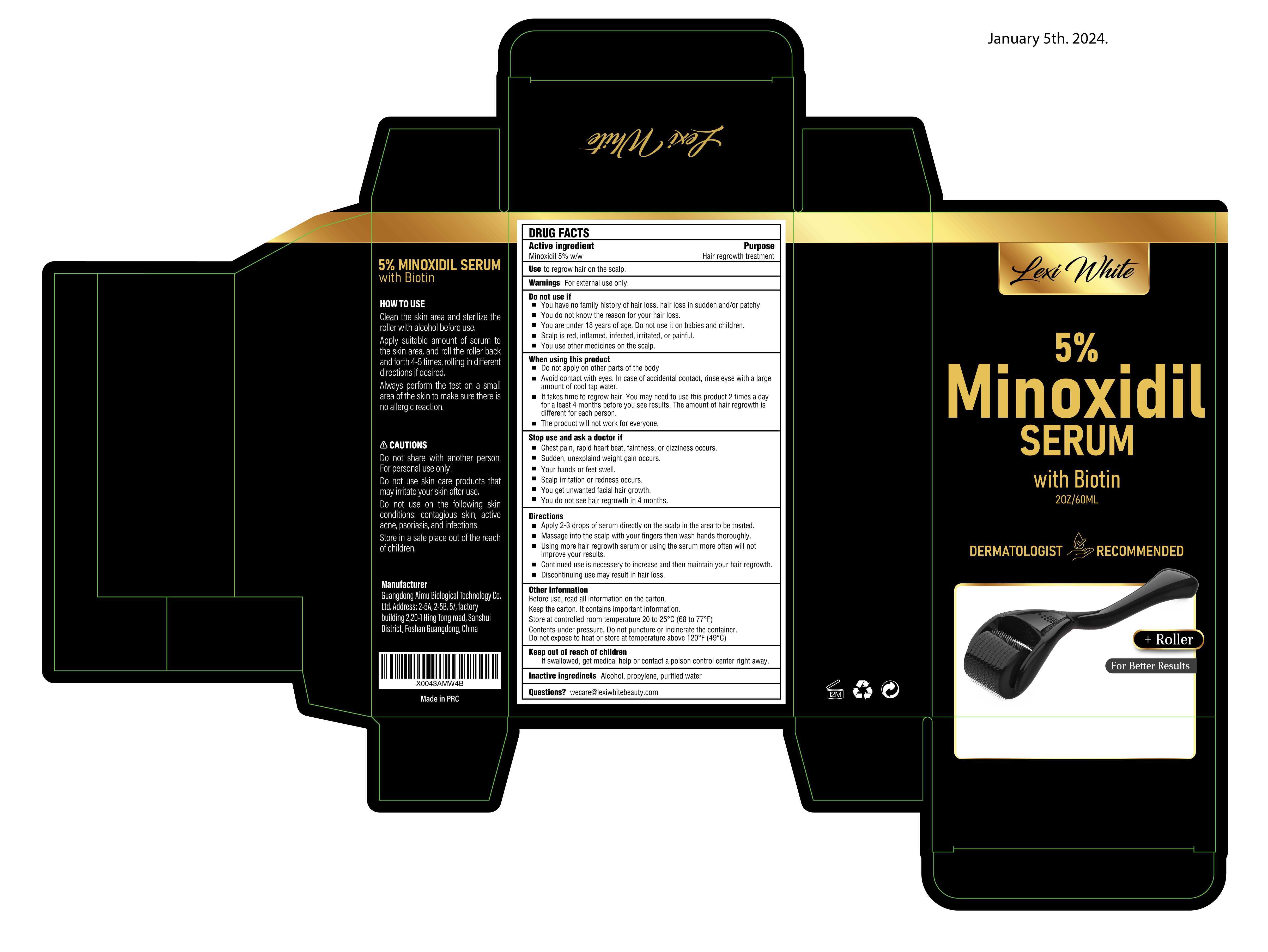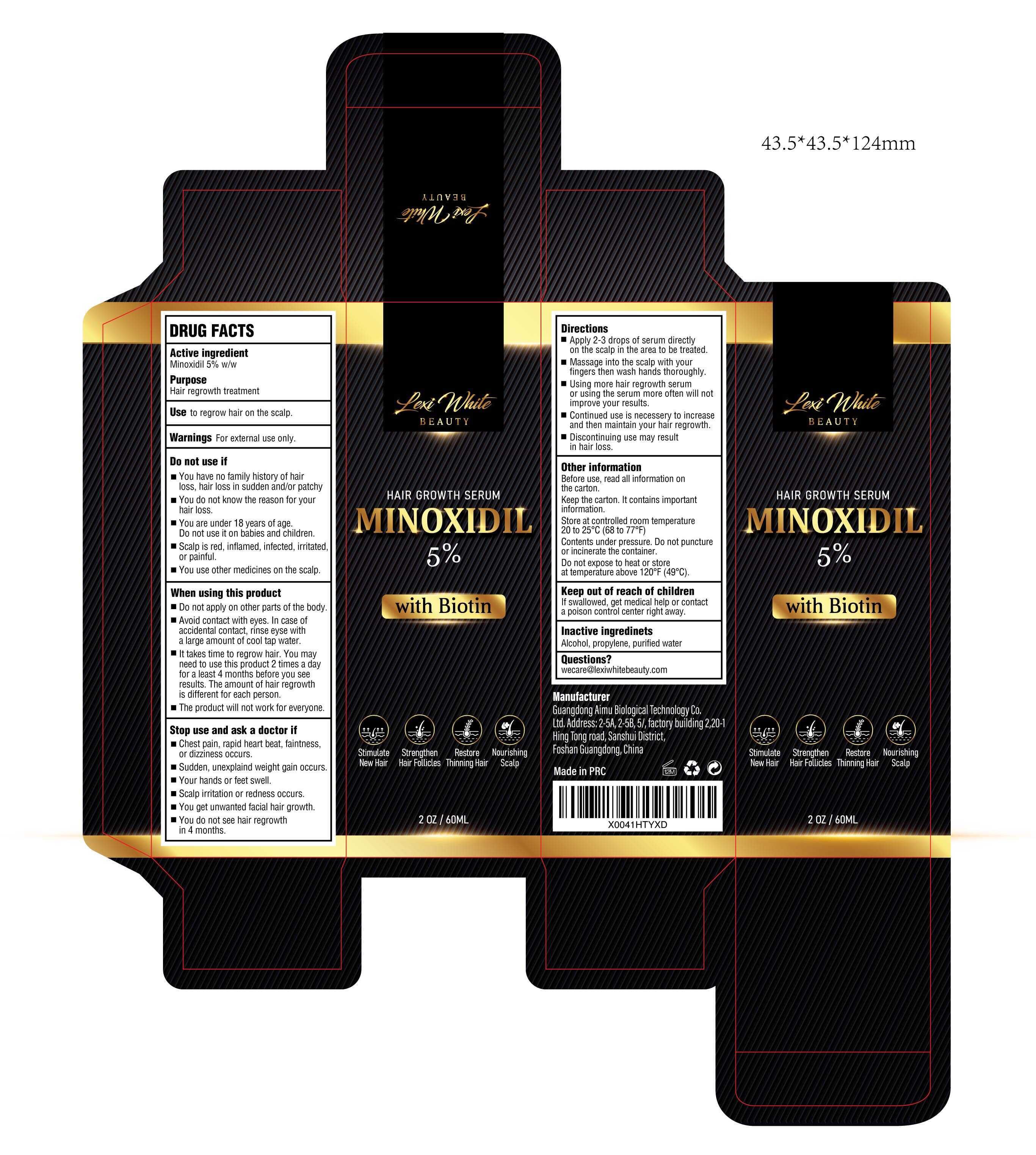 DRUG LABEL: Lexi White Beauty 5%  Minoxidil Serum
NDC: 83566-401 | Form: LIQUID
Manufacturer: Guangdong Aimu Biological Technology Co., Ltd
Category: otc | Type: HUMAN OTC DRUG LABEL
Date: 20240415

ACTIVE INGREDIENTS: MINOXIDIL 5 g/100 mL
INACTIVE INGREDIENTS: ALCOHOL; WATER; PROPYLENE; BIOTIN

Lexi White Beauty 5% Minoxidil Serum

5% Minoxidil Serum

ACTIVE INGREDIENT

Minoxidil 5%

PURPOSE

Use to regrow hair on the scalp.

INDICATIONS AND USAGE

Apply 2-3 drops of serum directly on the scalp in the area to be treated.
Massage into the scalp with your fingers then wash hands thoroughly.
Using more hair regrowth serum or using the serum more often will not improve your results.
Continued use is necessery to increase and then maintain your hair regrowth.
Discontinuing use may result in hair loss.

WARNINGS

For external use only

DO NOT USE

You have no family history of hair loss, hair loss in sudden and/or patchy.
You do not know the reason for your hair loss.
You are under 18 years of age. Do not use it on babies and children.
Scalp is red, inflamed, infected, irritated, or painful.
You use other medicines on the scalp.

WHEN USING

Do not apply on other parts of the body.
Avoid contact with eyes. In case of accidental contact, rinse eyse with a largeamount of cool tap water.
lt takes time to regrow hair. You may need to use this product 2 times a day for a least 4 months before you see results. The amount of hair regrowth is different for each person.
The product will not work for everyone.

STOP USE

Chest pain,rapid heart beat, faintness,or dizziness occurs.
Sudden, unexplaind weight gain occurs.
Your hands or feet swel.
Scalp irritation or redness occurs.
You get unwanted facial hair growth.
You do not see hair regrowth in 4 months

KEEP OUT OF REACH OF CHILDREN

lf swallowed, get medical help or contact a poison control center right away.

DOSAGE AND ADMINISTRATION

Apply 2-3 drops of serum directly on the scalp in the area to be treated.

Massage into the scalp with your fingers then wash hands thoroughly.

STORAGE AND HANDLING

Store at controlled room temperature 20 to 25°C (68 to 77°F).
puncture or incinerate the container.Do not expose to heat or store at temperature above 120°F (49°C)

INACTIVE INGREDIENT

Alcohol,propylene, purified water